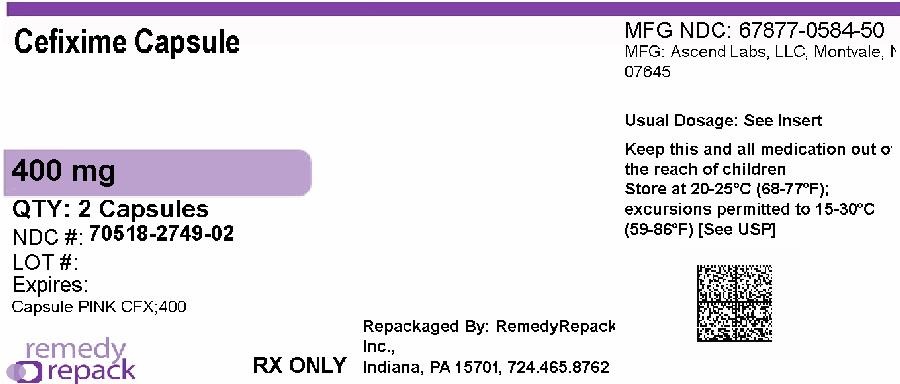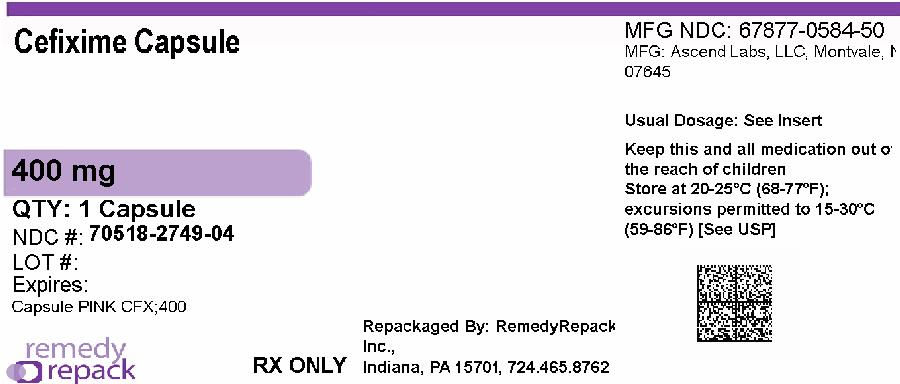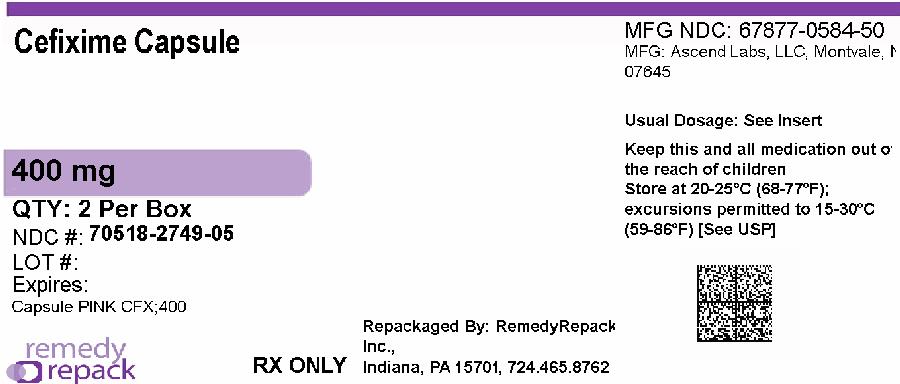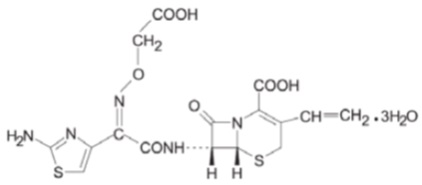 DRUG LABEL: CEFIXIME
NDC: 70518-2749 | Form: CAPSULE
Manufacturer: REMEDYREPACK INC.
Category: prescription | Type: HUMAN PRESCRIPTION DRUG LABEL
Date: 20260211

ACTIVE INGREDIENTS: CEFIXIME 400 mg/1 1
INACTIVE INGREDIENTS: CROSCARMELLOSE SODIUM; SILICON DIOXIDE; HYDROXYPROPYL CELLULOSE, LOW SUBSTITUTED; MAGNESIUM STEARATE; MANNITOL; ISOPROPYL ALCOHOL; BUTYL ALCOHOL; ALCOHOL; GELATIN; FERRIC OXIDE RED; POTASSIUM HYDROXIDE; PROPYLENE GLYCOL; SHELLAC; SODIUM LAURYL SULFATE; AMMONIA; TITANIUM DIOXIDE; FERROSOFERRIC OXIDE

HIGHLIGHTS OF PRESCRIBING INFORMATION

These highlights do not include all the information needed to use CEFIXIME CAPSULES safely and effectively. See full prescribing information for CEFIXIME CAPSULES.
CEFIXIME capsules, for oral use.
Initial U.S. Approval: 1986

1 INDICATIONS AND USAGE

Cefixime is a cephalosporin antibacterial drug indicated in the treatment of adults and pediatric six months and older with the following infections:

- Uncomplicated Urinary Tract Infections (1.1)
- Pharyngitis and Tonsillitis (1.3)
- Acute Exacerbations of Chronic Bronchitis (1.4)
- Uncomplicated Gonorrhea (cervical/urethral) (1.5)

To reduce the development of drug-resistant bacteria and maintain the effectiveness of cefixime and other antibacterial drugs, cefixime should be used only to treat infections that are proven or strongly suspected to be caused by bacteria.

2 DOSAGE AND ADMINISTRATION

· Adults: 400 mg daily (2.1)

3 DOSAGE FORMS AND STRENGTHS

· Capsules: 400 mg

4 CONTRAINDICATIONS

· Contraindicated in patients with known allergy to cefixime or other cephalosporins.

5 WARNINGS AND PRECAUTIONS

· Hypersensitivity reactions including shock and fatalities have been reported with cefixime. Discontinue use if a reaction occurs. (5.1)

· Clostridium difficile associated diarrhea: Evaluate if diarrhea occurs. (5.2)

6 ADVERSE REACTIONS

Most common adverse reactions are gastrointestinal such as diarrhea (16%), nausea (7%), loose stools (6%), abdominal pain (3%), dyspepsia (3%), and vomiting. (6)

To report SUSPECTED ADVERSE REACTIONS, contact Ascend Laboratories, LLC at 1-877-ASC-RX01 (877-272-7901) or FDA at 1-800-FDA-1088 or www.fda.gov/medwatch.

7 DRUG INTERACTIONS

· Elevated carbamazepine levels have been reported in postmarketing experience when cefixime is administered concomitantly. (7.1)

· Increased prothrombin time, with or without clinical bleeding, has been reported when cefixime is administered concomitantly with warfarin and anticoagulants. (7.2)

8 USE IN SPECIFIC POPULATIONS

· Pregnancy: Cefixime should be used during pregnancy only if clearly needed. (8.1)

· Nursing Mothers: Consideration should be given to discontinuing nursing temporarily during treatment with cefixime. (8.3)

· Children: Efficacy and safety in infants aged less than six months have not been established. (8.4)

· Geriatric Use: Clinical studies did not include sufficient numbers of subjects aged 65 and older to determine whether they respond differently than younger subjects. Other reported clinical experience has not identified differences in responses between the elderly and younger patients. (8.5)

· Renal Impairment: Cefixime may be administered in the presence of impaired renal function. Dose adjustment is required in patients whose creatinine clearance is less than 60 mL/min. (8.6)

FULL PRESCRIBING INFORMATION

1 INDICATIONS AND USAGE

1.1 Uncomplicated Urinary Tract Infections

Cefixime is indicated in the treatment of adults and pediatric patients six months of age or older with uncomplicated urinary tract infections caused by susceptible isolates of Escherichia coli and Proteus mirabilis.

1.3 Pharyngitis and Tonsillitis

Cefixime capsules are indicated in the treatment of adults and pediatric patients six months of age or older with pharyngitis and tonsillitis caused by susceptible isolates of Streptococcus pyogenes. (Note: Penicillin is the usual drug of choice in the treatment of Streptococcus pyogenes infections.

Cefixime capsules are generally effective in the eradication of Streptococcus pyogenes from the nasopharynx; however, data establishing the efficacy of cefixime capsules in the subsequent prevention of rheumatic fever is not available.)

1.4 Acute Exacerbations of Chronic Bronchitis

Cefixime capsules is indicated in the treatment of adults and pediatric patients six months of age or older with acute exacerbations of chronic bronchitis caused by susceptible isolates of Streptococcus pneumoniae and Haemophilus influenzae.

1.5 Uncomplicated Gonorrhea (cervical/urethral)

Cefixime capsules is indicated in the treatment of adults and pediatric patients six months of age or older with uncomplicated gonorrhea (cervical/urethral) caused by susceptible isolates of Neisseria gonorrhoeae (penicillinase-and non-penicillinase-producing isolates).

1.6 Usage

To reduce the development of drug resistant bacteria and maintain the effectiveness of cefixime capsules and other antibacterial drugs, cefixime capsules should be used only to treat infections that are proven or strongly suspected to be caused by susceptible bacteria. When culture and susceptibility information are available, they should be considered in selecting or modifying antimicrobial therapy. In the absence of such data, local epidemiology and susceptibility patterns may contribute to the empiric selection of therapy.

2 DOSAGE AND ADMINISTRATION

2.1 Adults

The recommended dose of cefixime is 400 mg daily. This may be given as a 400 mg capsule daily. For the treatment of uncomplicated cervical/urethral gonococcal infections, a single oral dose of 400 mg is recommended. The capsule may be administered without regard to food.

In the treatment of infections due to Streptococcus pyogenes, a therapeutic dosage of cefixime should be administered for at least 10 days.

2.2 Pediatric Patients (6 months or older)

The recommended dose is 8 mg/kg/day of the suspension. This may be administered as a single daily dose or may be given in two divided doses, as 4 mg/kg every 12 hours.
Note: A suggested dose has been determined for each pediatric weight range. Refer to Table 1. Ensure all orders that specify a dose in milliliters include a concentration, because cefixime for oral suspension is available in three different concentrations (100 mg/5 mL, 200 mg/5 mL, and 500 mg/5 mL).
Table 1. Suggested doses for pediatric patients

PEDIATRIC DOSAGE CHART
Doses are suggested for each weight range and rounded for ease of administration
 |  | Cefixime for Oral Suspension
 |  | 100 mg/ 5 mL | 200 mg/ 5 mL | 500 mg/ 5 mL
Patient Weight (kg) | Dose/Day (mg) | Dose/Day (mL) | Dose/Day (mL) | Dose/Day (mL)
5 to 7.5* | 50 | 2.5 | -- | -
7.6 to 10* | 80 | 4 | 2 | -
10.1 to 12.5 | 100 | 5 | 2.5 | 1
12.6 to 20.5 | 150 | 7.5 | 4 | 1.5
20.6 to 28 | 200 | 10 | 5 | 2
28.1 to 33 | 250 | 12.5 | 6 | 2.5
33.1 to 40 | 300 | 15 | 7.5 | 3
40.1to 45 | 350 | 17.5 | 9 | 3.5
45.1 or greater | 400 | 20 | 10 | 4
* The preferred concentrations of oral suspension to use are 100 mg/5 mL or 200 mg/5 mL for pediatric patients in these weight ranges.

Children weighing more than 45 kg or older than 12 years should be treated with the recommended adult dose.
In the treatment of infections due to Streptococcus pyogenes, a therapeutic dosage of cefixime should be administered for at least 10 days.

2.3 Renal Impairment

Normal dose and schedule may be employed in patients with creatinine clearances of 60 mL/min or greater. Neither hemodialysis nor peritoneal dialysis removes significant amounts of drug from the body.

3 DOSAGE FORMS AND STRENGTHS

Cefixime Capsules are available for oral administration in the following dosage strength:

- Capsules provide 400 mg of cefixime as trihydrate. These are off white to yellow colour granular powder filled in size ''0''' hard gelatin capsules, pink opaque cap imprinted ''CFX'' with black ink and pink opaque body imprinted ''400'' with black ink.

4 CONTRAINDICATIONS

Cefixime capsules are contraindicated in patients with known allergy to cefixime or other cephalosporins.

5 WARNINGS AND PRECAUTIONS

5.1 Hypersensitivity Reactions

Anaphylactic/anaphylactoid reactions (including shock and fatalities) have been reported with the use of cefixime.

Before therapy with cefixime is instituted, careful inquiry should be made to determine whether the patient has had previous hypersensitivity reactions to cephalosporins, penicillins, or other drugs. If this product is to be given to penicillin-sensitive patients, caution should be exercised because cross hypersensitivity among beta-lactam antibiotics has been clearly documented and may occur in up to 10% of patients with a history of penicillin allergy. If an allergic reaction to cefixime occurs, discontinue the drug.

5.2 Clostridium difficile-Associated Diarrhea

Clostridium difficile associated diarrhea (CDAD) has been reported with use of nearly all antibacterial agents, including cefixime, and may range in severity from mild diarrhea to fatal colitis. Treatment with antibacterial agents alters the normal flora of the colon leading to overgrowth of C. difficile.

C. difficile produces toxins A and B which contribute to the development of CDAD. Hypertoxin producing isolates of C. difficile cause increased morbidity and mortality, as these infections can be refractory to antimicrobial therapy and may require colectomy. CDAD must be considered in all patients who present with diarrhea following antibacterial use. Careful medical history is necessary since CDAD has been reported to occur over two months after the administration of antibacterial agents.

If CDAD is suspected or confirmed, ongoing antibacterial use not directed against C. difficile may need to be discontinued. Appropriate fluid and electrolyte management, protein supplementation, antibacterial treatment of C. difficile, and surgical evaluation should be instituted as clinically indicated.

5.3 Dose Adjustment in Renal Impairment

The dose of cefixime should be adjusted in patients with renal impairment as well as those undergoing continuous ambulatory peritoneal dialysis (CAPD) and hemodialysis (HD). Patients on dialysis should be monitored carefully [see DOSAGE AND ADMINISTRATION (2)] .

5.4 Coagulation Effects

Cephalosporins, including cefixime, may be associated with a fall in prothrombin activity. Those at risk include patients with renal or hepatic impairment, or poor nutritional state, as well as patients receiving a protracted course of antimicrobial therapy, and patients previously stabilized on anticoagulant therapy. Prothrombin time should be monitored in patients at risk and exogenous vitamin K administered as indicated.

5.5 Development of Drug-Resistant Bacteria

Prescribing cefixime in the absence of a proven or strongly suspected bacterial infection is unlikely to provide benefit to the patient and increases the risk of the development of drug-resistant bacteria.

6 ADVERSE REACTIONS

6.1 Clinical Trials Experience

Because clinical trials are conducted under widely varying conditions, adverse reaction rates observed in the clinical trials of a drug cannot be directly compared to rates in the clinical trials of another drug and may not reflect the rates observed in practice.

The most commonly seen adverse reactions in U.S. trials of the tablet formulation were gastrointestinal events, which were reported in 30% of adult patients on either the twice daily or the once daily regimen. Five percent (5%) of patients in the U.S. clinical trials discontinued therapy because of drug-related adverse reactions. Individual adverse reactions included diarrhea 16%, loose or frequent stools 6%, abdominal pain 3%, nausea 7%, dyspepsia 3%, and flatulence 4%. The incidence of gastrointestinal adverse reactions, including diarrhea and loose stools, in pediatric patients receiving the suspension was comparable to the incidence seen in adult patients receiving tablets.

6.2 Post-marketing Experience

The following adverse reactions have been reported following the post-approval use of cefixime. Incidence rates were less than 1 in 50 (less than 2%).

Gastrointestinal

Several cases of documented pseudomembranous colitis were identified in clinical trials. The onset of pseudomembranous colitis symptoms may occur during or after therapy.

Hypersensitivity Reactions

Anaphylactic/anaphylactoid reactions (including shock and fatalities), skin rashes, urticaria, drug fever, pruritus, angioedema, and facial edema. Erythema multiforme, Stevens-Johnson syndrome, and serum sickness-like reactions have been reported.

Hepatic

Transient elevations in SGPT, SGOT, alkaline phosphatase, hepatitis, jaundice.

Renal

Transient elevations in BUN or creatinine, acute renal failure.

Central Nervous System

Headaches, dizziness, seizures.

Hemic and Lymphatic System

Transient thrombocytopenia, leukopenia, neutropenia, prolongation in prothrombin time, elevated LDH, pancytopenia, agranulocytosis, and eosinophilia.

Abnormal Laboratory Tests

Hyperbilirubinemia.

Other Adverse Reactions

Genital pruritus, vaginitis, candidiasis, toxic epidermal necrolysis.

Adverse Reactions Reported for Cephalosporin-class Drugs

Allergic reactions, superinfection, renal dysfunction, toxic nephropathy, hepatic dysfunction including cholestasis, aplastic anemia, hemolytic anemia, hemorrhage, and colitis.

Several cephalosporins have been implicated in triggering seizures, particularly in patients with renal impairment when the dosage was not reduced [see Dosage and Administration (2) and Overdosage (10)] . If seizures associated with drug therapy occur, the drug should be discontinued. Anticonvulsant therapy can be given if clinically indicated.

7 DRUG INTERACTIONS

7.1 Carbamazepine

Elevated carbamazepine levels have been reported in postmarketing experience when cefixime is administered concomitantly. Drug monitoring may be of assistance in detecting alterations in carbamazepine plasma concentrations.

7.2 Warfarin and Anticoagulants

Increased prothrombin time, with or without clinical bleeding, has been reported when cefixime is administered concomitantly.

7.3 Drug/Laboratory Test Interactions

A false-positive reaction for ketones in the urine may occur with tests using nitroprusside but not with those using nitroferricyanide.

The administration of cefixime may result in a false-positive reaction for glucose in the urine using Clinitest®**, Benedict’s solution, or Fehling’s solution. It is recommended that glucose tests based on enzymatic glucose oxidase reactions (such as Clinistix®** or TesTape®**) be used. A false-positive direct Coombs test has been reported during treatment with other cephalosporins; therefore, it should be recognized that a positive Coombs test may be due to the drug.

**Clinitest® and Clinistix® are registered trademarks of Ames Division, Miles Laboratories, Inc. Tes-Tape® is a registered trademark of Eli Lilly and Company.

8 USE IN SPECIFIC POPULATIONS

8.1 Pregnancy

Pregnancy Category B

Pregnancy Category B. Reproduction studies have been performed in mice and rats at doses up to 40 times the human dose and have revealed no evidence of harm to the fetus due to cefixime. There are no adequate and well-controlled studies in pregnant women. Because animal reproduction studies are not always predictive of human response, this drug should be used during pregnancy only if clearly needed.

8.2 Labor and Delivery

Cefixime has not been studied for use during labor and delivery. Treatment should only be given if clearly needed.

8.3 Nursing Mothers

It is not known whether cefixime is excreted in human milk. Consideration should be given to discontinuing nursing temporarily during treatment with this drug.

8.4 Pediatric Use

Safety and effectiveness of cefixime in children aged less than six months old have not been established. The incidence of gastrointestinal adverse reactions, including diarrhea and loose stools, in the pediatric patients receiving the suspension, was comparable to the incidence seen in adult patients receiving tablets.

8.5 Geriatric Use

Clinical studies did not include sufficient numbers of subjects aged 65 and older to determine whether they respond differently than younger subjects. Other reported clinical experience has not identified differences in responses between the elderly and younger patients. A pharmacokinetic study in the elderly detected differences in pharmacokinetic parameters [see Clinical Pharmacology (12.3)] . These differences were small and do not indicate a need for dosage adjustment of the drug in the elderly.

8.6 Renal Impairment

The dose of cefixime should be adjusted in patients with renal impairment as well as those undergoing continuous ambulatory peritoneal dialysis (CAPD) and hemodialysis (HD). Patients on dialysis should be monitored carefully [see Dosage and Administration (2.3)] .

10 OVERDOSAGE

Gastric lavage may be indicated; otherwise, no specific antidote exists. Cefixime is not removed in significant quantities from the circulation by hemodialysis or peritoneal dialysis. Adverse reactions in small numbers of healthy adult volunteers receiving single doses up to 2 g of cefixime did not differ from the profile seen in patients treated at the recommended doses.

11 DESCRIPTION

Cefixime is a semisynthetic, cephalosporin antibacterial for oral administration. Chemically, it is (6R,7R)-7-[2-(2-Amino-4-thiazolyl)glyoxylamido]-8-oxo-3-vinyl-5-thia-1-azabicyclo [4.2.0] oct-2-ene-2-carboxylic acid, 7^2-(Z)-[ O-(carboxy methyl) oxime] trihydrate.

Molecular weight = 507.50 as the trihydrate. Chemical Formula is C16H15N5O7S2.3H2O

The structural formula for cefixime is:

- I nactive ingredients contained in cefixime capsules 400 mg are: colloidal silicon dioxide, croscarmellose sodium, low substituted hydroxypropyl cellulose, magnesium stearate and mannitol. The capsule shell contains the following inactive ingredients: black iron oxide, butyl alcohol, dehydrated alcohol, gelatin, iron oxide red, isopropyl alcohol, potassium hydroxide, propylene glycol, shellac, sodium lauryl sulphate, strong ammonia solution and titanium dioxide.

12 CLINICAL PHARMACOLOGY

12.1 Mechanism of Action

Cefixime is a semisynthetic cephalosporin antibacterial drug [see Microbiology (12.4)] .

12.3 Pharmacokinetics

Cefixime tablets and suspension, given orally, are about 40% to 50% absorbed whether administered with or without food; however, time to maximal absorption is increased approximately 0.8 hours when administered with food. A single 200 mg tablet of cefixime produces an average peak serum concentration of approximately 2 mcg/mL (range 1 to 4 mcg/mL); a single 400 mg tablet produces an average peak concentration of approximately 3.7 mcg/mL (range 1.3 to 7.7 mcg/mL). The oral suspension produces average peak concentrations approximately 25% to 50% higher than the tablets, when tested in normal adult volunteers. Two hundred and 400 mg doses of oral suspension produce average peak concentrations of 3 mcg/mL (range 1 to 4.5 mcg/mL) and 4.6 mcg/mL (range 1.9 to 7.7 mcg/mL), respectively, when tested in normal adult volunteers. The area under the time versus concentration curve (AUC) is greater by approximately 10% to 25% with the oral suspension than with the tablet after doses of 100 to 400 mg, when tested in normal adult volunteers. This increased absorption should be taken into consideration if the oral suspension is to be substituted for the tablet. Crossover studies of tablet versus suspension have not been performed in children.

The 400 mg capsule is bioequivalent to the 400 mg tablet under fasting conditions. However, food reduces the absorption following administration of the capsule by approximately 15% based on AUC and 25% based on Cmax.

Peak serum concentrations occur between 2 and 6 hours following oral administration of a single 200 mg tablet, a single 400 mg tablet or 400 mg of cefixime suspension. Peak serum concentrations occur between 2 and 5 hours following a single administration of 200 mg of suspension. Peak serum concentrations occur between 3 and 8 hours following oral administration of a single 400 mg capsule.

Distribution

Serum protein binding is concentration independent with a bound fraction of approximately 65%. In a multiple dose study conducted with a research formulation which is less bioavailable than the tablet or suspension, there was little accumulation of drug in serum or urine after dosing for 14 days. Adequate data on CSF levels of cefixime are not available.

Metabolism and Excretion

There is no evidence of metabolism of cefixime in vivo. Approximately 50% of the absorbed dose is excreted unchanged in the urine in 24 hours. In animal studies, it was noted that cefixime is also excreted in the bile in excess of 10% of the administered dose. The serum half-life of cefixime in healthy subjects is independent of dosage form and averages 3 to 4 hours but may range up to 9 hours in some normal volunteers.

Special Populations

Geriatrics: Average AUCs at steady state in elderly patients are approximately 40% higher than average AUCs in other healthy adults. Differences in the pharmacokinetic parameters between 12 young and 12 elderly subjects who received 400 mg of cefixime once daily for 5 days are summarized as follows:

Pharmacokinetic Parameters (mean ± SD) for Cefixime in Both Young & Elderly Subjects
Pharmacokinetic parameter | Young | Elderly
Cmax (mg/L) | 4.74 ± 1.43 | 5.68 ± 1.83
Tmax (h)* | 3.9 ± 0.3 | 4.3 ± 0.6
AUC (mg.h/L)* | 34.9 ± 12.2 | 49.5 ± 19.1
T½ (h)* | 3.5 ± 0.6 | 4.2 ± 0.4
Cave (mg/L)* | 1.42 ±0.50 | 1.99 ± 0.75
*Difference between age groups was significant. (p<0.05)

However, these increases were not clinically significant [see Dosage and Administration (2)] .

Renal Impairment: In subjects with moderate impairment of renal function (20 to 40 mL/min creatinine clearance), the average serum half-life of cefixime is prolonged to 6.4 hours. In severe renal impairment (5 to 20 mL/min creatinine clearance), the half-life increased to an average of 11.5 hours. The drug is not cleared significantly from the blood by hemodialysis or peritoneal dialysis. However, a study indicated that with doses of 400 mg, patients undergoing hemodialysis have similar blood profiles as subjects with creatinine clearances of 21 to 60 mL/min.

12.4 Microbiology

Mechanism of Action

As with other cephalosporins, the bactericidal action of cefixime results from inhibition of cell wall synthesis. Cefixime is stable in the presence of certain beta-lactamase enzymes. As a result, certain organisms resistant to penicillins and some cephalosporins due to the presence of beta-lactamases may be susceptible to cefixime.

Resistance

Resistance to cefixime in isolates of Haemophilus influenzae and Neisseria gonorrhoeae is most often associated with alterations in penicillin-binding proteins (PBPs). Cefixime may have limited activity against Enterobacteriaceae producing extended spectrum beta-lactamases (ESBLs). Pseudomonas species, Enterococcus species, strains of Group D streptococci, Listeria monocytogenes, most strains of staphylococci (including methicillin-resistant strains), most strains of Enterobacter species, most strains of Bacteroides fragilis, and most strains of Clostridium species are resistant to cefixime.

Antimicrobial Activity

Cefixime has been shown to be active against most isolates of the following microorganisms, both in vitro and in clinical infections [see Indications And Usage (1).

Gram-positive Bacteria

Streptococcus pneumoniae

Streptococcus pyogenes

Gram-negative Bacteria

Escherichia coli

Haemophilus influenzae

Moraxella catarrhalis

Neisseria gonorrhoeae

Proteus mirabilis

The following in vitro data are available, but their clinical significance is unknown. At least 90 percent of the following bacteria exhibit an in vitro minimum inhibitory concentration (MIC) less than or equal to the susceptible breakpoint for cefixime against isolates of similar genus or organism group. However, the efficacy of cefixime in treating clinical infections caused by to these bacteria has not been established in adequate and well-controlled clinical trials.

Gram-positive Bacteria

Streptococcus agalactiae

Gram-negative Bacteria

Citrobacter amalonaticus

Citrobacter diversus

Haemophilus parainfluenzae

Klebsiella oxytoca

Klebsiella pneumoniae

Pasteurella multocida

Proteus vulgaris

Providencia species

Salmonella species

Serratia marcescens

Shigella species

Susceptibility Testing

For specific information regarding susceptibility test interpretive criteria and associated test methods and quality control standards recognized by FDA for this drug, please see: https://www.fda.gov/STIC.

13 NONCLINICAL TOXICOLOGY

13.1 Carcinogenesis, Mutagenesis, Impairment of Fertility

Lifetime studies in animals to evaluate carcinogenic potential have not been conducted. Cefixime did not cause point mutations in bacteria or mammalian cells, DNA damage, or chromosome damage in vitro and did not exhibit clastogenic potential in vivo in the mouse micronucleus test. In rats, fertility and reproductive performance were not affected by cefixime at doses up to 25 times the adult therapeutic dose.

16 HOW SUPPLIED/STORAGE AND HANDLING

Cefixime Capsules 400 mg

Off white to yellow color granular powder filled in size “0” hard gelatin capsules, pink opaque cap imprinted “CFX” with black ink and pink opaque body imprinted “400” with black ink.

NDC: 70518-2749-00

NDC: 70518-2749-01

NDC: 70518-2749-02

NDC: 70518-2749-03

NDC: 70518-2749-04

NDC: 70518-2749-05

PACKAGING: 10 in 1 BOTTLE PLASTIC

PACKAGING: 1 in 1 BOTTLE PLASTIC

PACKAGING: 2 in 1 BOTTLE PLASTIC

PACKAGING: 2 in 1 BLISTER PACK

PACKAGING: 2 in 1 BOX

PACKAGING: 1 in 1 POUCH

Store at 20°C to 25°C (68°F to 77°F) [See USP Controlled Room Temperature

Repackaged and Distributed By:

Remedy Repack, Inc.

625 Kolter Dr. Suite #4 Indiana, PA 1-724-465-8762

17 PATIENT COUNSELING INFORMATION

17.1 Information for Patients

Patients should be counseled that antibacterial drugs, including cefixime, should only be used to treat bacterial infections. They do not treat viral infections (e.g., the common cold). When cefixime is prescribed to treat a bacterial infection, patients should be told that although it is common to feel better early in the course of therapy, the medication should be taken exactly as directed. Skipping doses or not completing the full course of therapy may: (1) decrease the effectiveness of the immediate treatment and (2) increase the likelihood that bacteria will develop resistance and will not be treatable by cefixime or other antibacterial drugs in the future.

Diarrhea is a common problem caused by antibiotics which usually ends when the antibiotic is discontinued. Sometimes after starting treatment with antibiotics, patients can develop watery and bloody stools (with or without stomach cramps and fever) even as late as two or more months after having taken the last dose of the antibiotic. If this occurs, patients should contact their physician as soon as possible.

Repackaged and Distributed By:

Remedy Repack, Inc.

625 Kolter Dr. Suite #4 Indiana, PA 1-724-465-8762

PACKAGE LABEL

DRUG: CEFIXIME

GENERIC: CEFIXIME

DOSAGE: CAPSULE

ADMINSTRATION: ORAL

NDC: 70518-2749-0

NDC: 70518-2749-1

NDC: 70518-2749-2

NDC: 70518-2749-3

NDC: 70518-2749-4

COLOR: pink

SHAPE: CAPSULE

SCORE: No score

SIZE: 21 mm

IMPRINT: CFX;400

PACKAGING: 10 in 1 BOTTLE, PLASTIC

PACKAGING: 1 in 1 BOTTLE PLASTIC

PACKAGING: 2 in 1 BOTTLE PLASTIC

PACKAGING: 2 in 1 BLISTER PACK

PACKAGING: 1 in 1 POUCH

PACKAGING: 2 in 1 BOX

ACTIVE INGREDIENT(S):

- CEFIXIME 400mg in 1

INACTIVE INGREDIENT(S):

- SILICON DIOXIDE
- AMMONIA
- SODIUM LAURYL SULFATE
- SHELLAC
- PROPYLENE GLYCOL
- POTASSIUM HYDROXIDE
- FERRIC OXIDE RED
- TITANIUM DIOXIDE
- GELATIN
- BUTYL ALCOHOL
- ISOPROPYL ALCOHOL
- MANNITOL
- MAGNESIUM STEARATE
- HYDROXYPROPYL CELLULOSE, LOW SUBSTITUTED
- CROSCARMELLOSE SODIUM
- ALCOHOL
- FERROSOFERRIC OXIDE